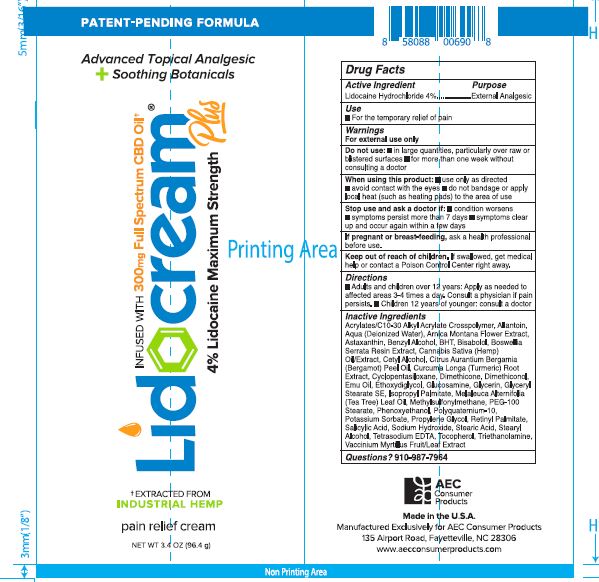 DRUG LABEL: pain relief cream
NDC: 86089-222 | Form: CREAM
Manufacturer: AEC Consumer Products
Category: otc | Type: HUMAN OTC DRUG LABEL
Date: 20210105

ACTIVE INGREDIENTS: LIDOCAINE HYDROCHLORIDE 3.86 g/100 g
INACTIVE INGREDIENTS: ALLANTOIN; water; ARNICA MONTANA FLOWER; ASTAXANTHIN; BENZYL ALCOHOL; BISABOLOL OXIDE A; CANNABIS SATIVA SEED OIL; CETYL ALCOHOL; CITRUS AURANTIIFOLIA FRUIT OIL; CURCUMA LONGA LEAF; DIMETHICONE; EMU OIL; ETHOXYDIGLYCOL BEHENATE; GLUCOSAMINE; GLYCERYL STEARATE SE; ISOPROPYL PALMITATE; MELALEUCA ALTERNIFOLIA LEAF; PEG-100 STEARATE; PHENOXYETHANOL; POLYQUATERNIUM-10 (1000 MPA.S AT 2%); POTASSIUM SORBATE; PROPYLENE GLYCOL; SODIUM HYDROXIDE; STEARIC ACID; STEARYL ALCOHOL; TETRASODIUM DIETHYLENETRIAMINEPENTAMETHYLENEPHOSPHONATE; TOCOPHEROL; VACCINIUM MYRTILLUS LEAF

Drug Facts

Active Ingredient Purpose
Lidocaine Hydrochloride 4%.......................................................................External Analgesic

Purpose

External Analgesic

Warning

For External use only

When using this product use only as directed

- avoid contact with the eyes
- do not bandage or apply local heat (such as heating pads) to the area of use

Stop use and ask a doctor if condition worsens symptoms persist more than 7 days

symptoms clear up and occur again with a few days

Keep out of use of children. If swallowed, get medical help or contact a Poison Control Center right away

Storage and Handling

Apply as needed to affectedareas 3-4 times a day.

Inactive Ingredients

Acrylates/C10-30 Alkyl Acrylate Crosspolymer, Allantoin, Aqua, Arnica Mountain Flower Extract, Astaxanthin, Benzyl Alcohol, BHT, Bisabolol, Boswellia Serrata Resin Extract, Cannabis Sativa Oil/Extract, Cetyl Alcohol, Citrus Aurantium Bergamia Peel Oil, Curcurria Longa Root Extract, Cyclopentasiloxane, Dimethicone, Dimethicol, Emu Oil, Ethoxydiglycol, Glucosamine, Glycerin, Glyceryl Stearate SE, Isopropyl Palmitate, Melaleuca Alternifolia Leaf Oil, Methylsulfonylmethane, PEG-100 Stearate, Phenoxyethanol, Polyquaterium-10, Potassium Sorbate, Propylene Glycol, Retinyl Palmitate, Salicylic Acid, Sodium Hydroxide, Stearic Acid, Stearyl Alcohol, Tetrasodium EDTA, Tocopherol, Triethanolamine, Vaccinium Myrtillus Fruit/Leaf Extract

Indications

Use

For the temporary relief of pain

Do not use in large quantities, particularly over raw or blistered surfaces for more than one week without consulting a doctor

Ask a doctor if condition worsens symptoms persist more than 7 days symptoms clear up and occur again with a few days

Directions

Adults and children over 12 years: apply as needed to affected areas 3-4 times a day. Consult a physician if pain persists.

dosage

Apply as needed to affected areas 3-4 times a day.